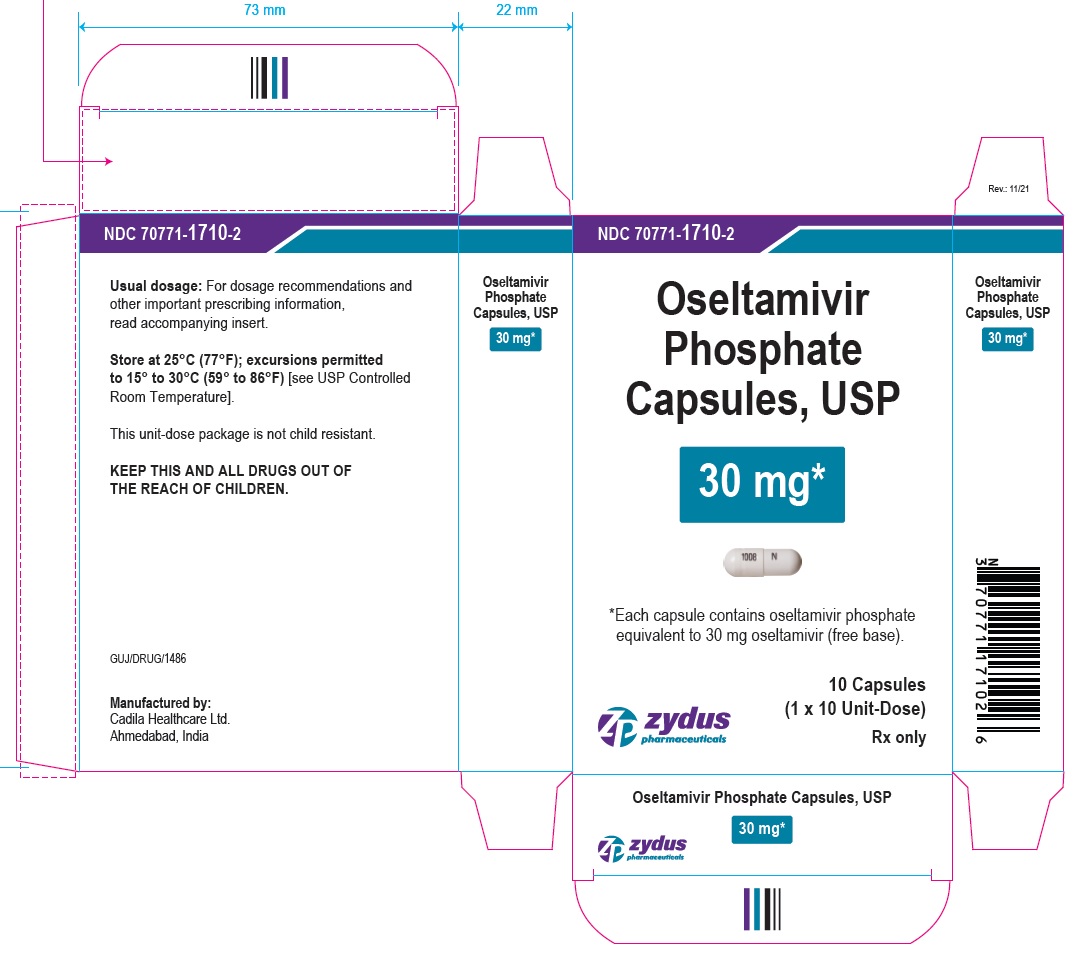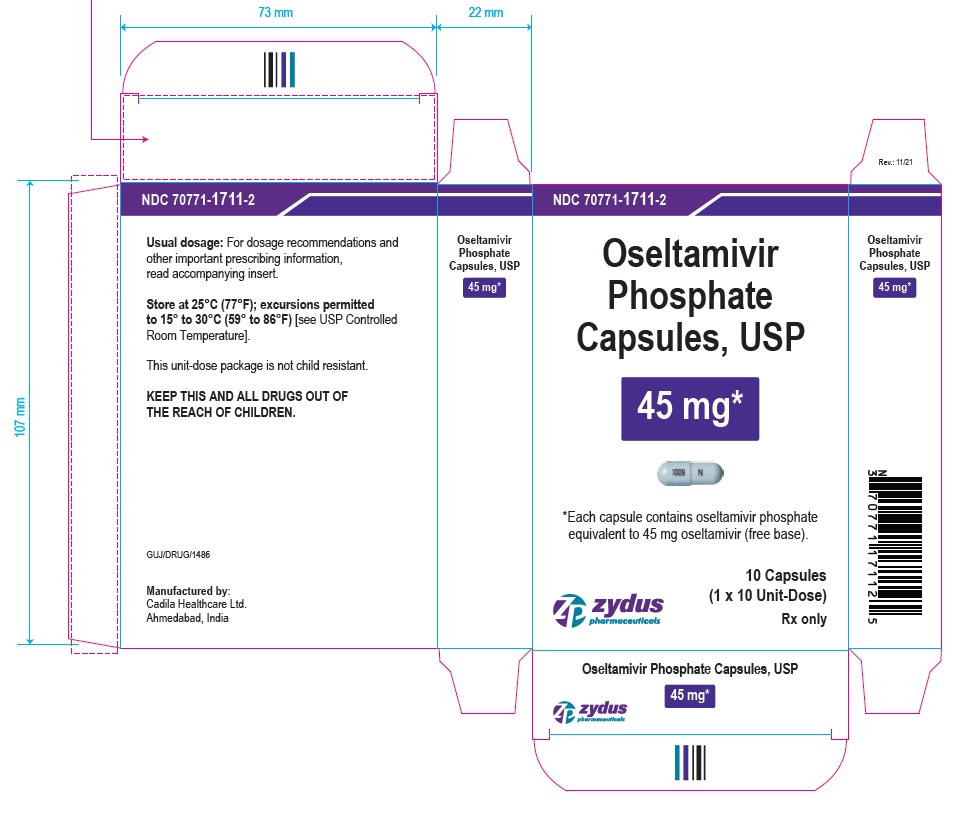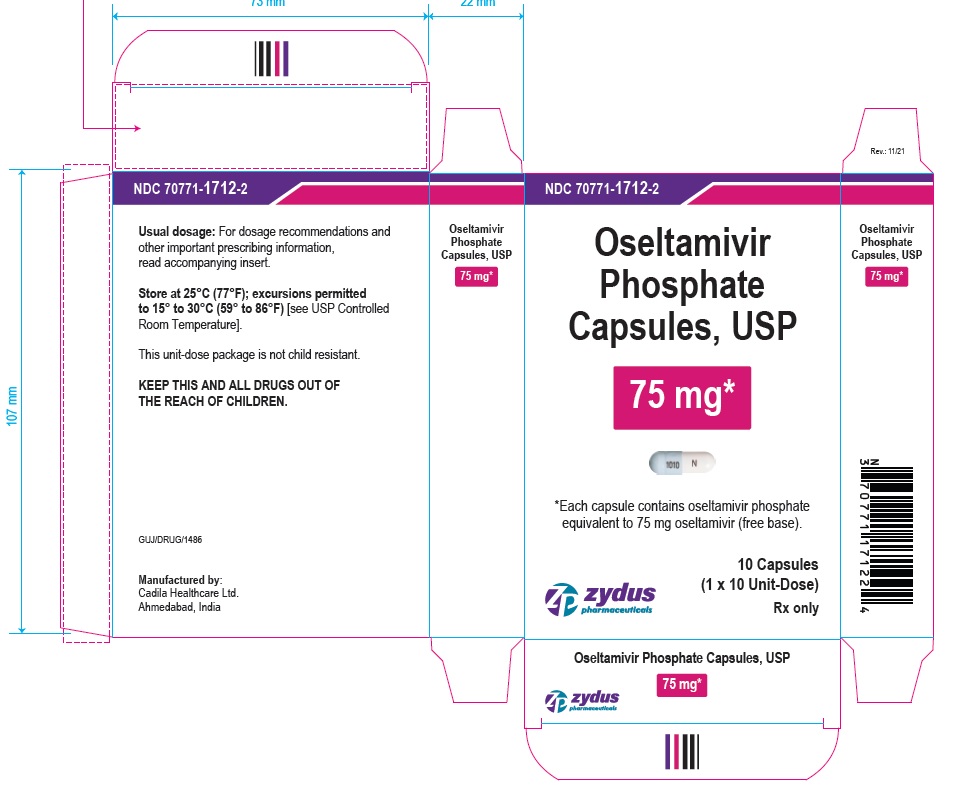 DRUG LABEL: OSELTAMIVIR PHOSPHATE
NDC: 70771-1710 | Form: CAPSULE
Manufacturer: Zydus Lifesciences Limited
Category: prescription | Type: HUMAN PRESCRIPTION DRUG LABEL
Date: 20241203

ACTIVE INGREDIENTS: OSELTAMIVIR PHOSPHATE 30 mg/1 1
INACTIVE INGREDIENTS: CROSCARMELLOSE SODIUM; FERROSOFERRIC OXIDE; GELATIN; POVIDONE K30; SODIUM LAURYL SULFATE; SODIUM STEARYL FUMARATE; STARCH, CORN; TALC; TITANIUM DIOXIDE; WATER

Oseltamivir Phosphate Capsules, USP

PACKAGE LABEL.PRINCIPAL DISPLAY PANEL

NDC 70771-1710-2

OSELTAMIVIR PHOSPHATE Capsules, USP

30* mg

*Each capsule contains oseltamivir phosphate equivalent to 30 mg oseltamivir (free base).

10 Capsules

(1 x 10 Unit-Dose)

Rx only

NDC 70771-1711-2

OSELTAMIVIR PHOSPHATE Capsules, USP

45* mg

*Each capsule contains oseltamivir phosphate equivalent to 45 mg oseltamivir (free base).

10 Capsules

(1 x 10 Unit-Dose)

Rx only

NDC 70771-1712-2

OSELTAMIVIR PHOSPHATE Capsules, USP

75* mg

*Each capsule contains oseltamivir phosphate equivalent to 75 mg oseltamivir (free base).

10 Capsules

(1 x 10 Unit-Dose)

Rx only